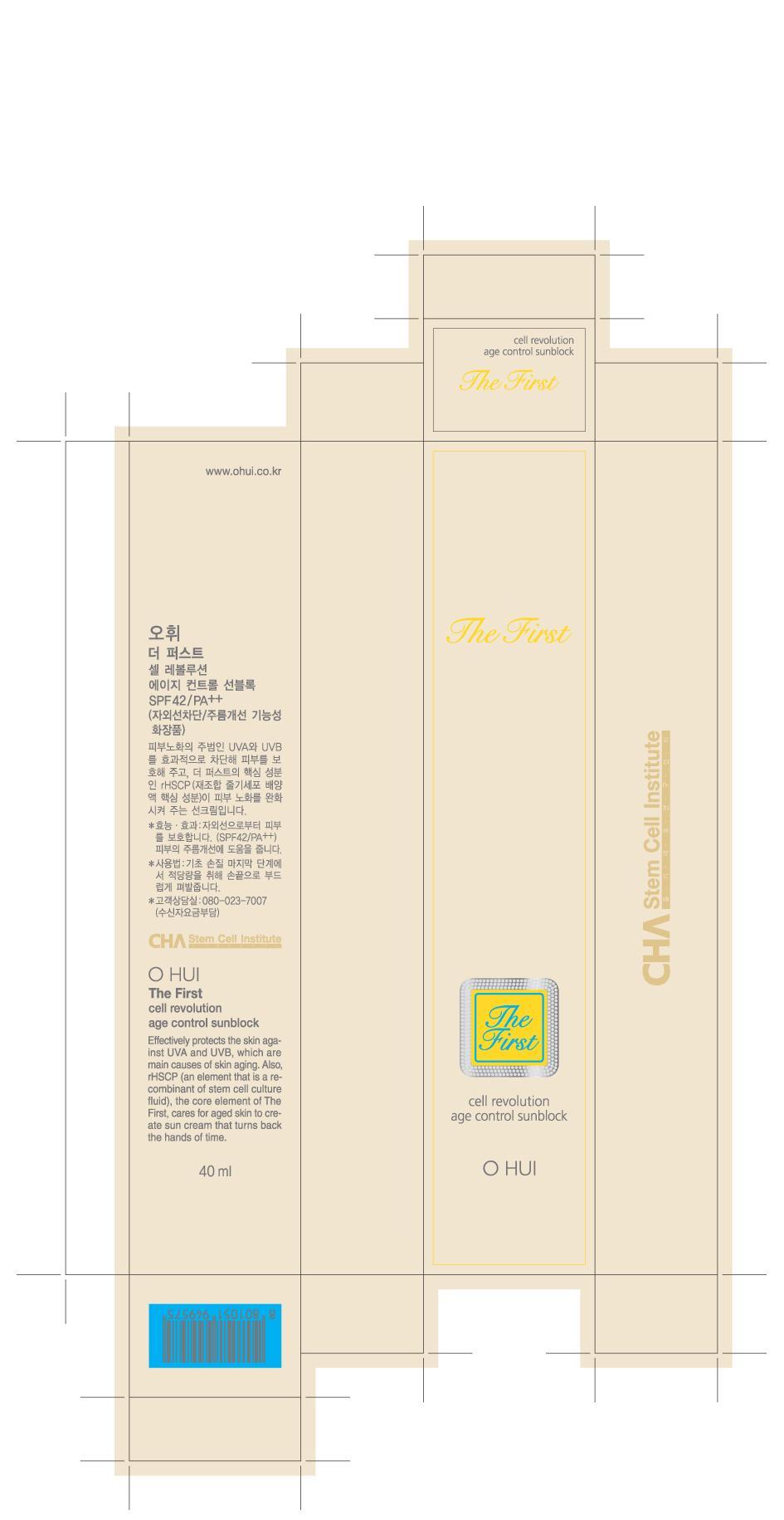 DRUG LABEL: OHUI THE FIRST CELL REVOLUTION AGE CONTROL SUN BLOCK
NDC: 53208-515 | Form: CREAM
Manufacturer: LG Household and Healthcare, Inc.
Category: otc | Type: HUMAN OTC DRUG LABEL
Date: 20110328

ACTIVE INGREDIENTS: OCTINOXATE 7 g/100 g; TITANIUM DIOXIDE 6 g/100 g; OCTISALATE 4.8 g/100 g; ENSULIZOLE 3.9 g/100 g; DIETHYLAMINO HYDROXYBENZOYL HEXYL BENZOATE 0.5 g/100 g; HYDROXYPROLINE 0.5 g/100 g
INACTIVE INGREDIENTS: WATER; CYCLOMETHICONE 5; BUTYLENE GLYCOL; GLYCERIN; CETOSTEARYL ALCOHOL; CETYL ETHYLHEXANOATE; BIOSACCHARIDE GUM-1; ALCOHOL; ISODODECANE; PANTHENOL; METHYL METHACRYLATE; INULIN; STEARIC ACID; TROMETHAMINE; CETYL PHOSPHATE; PHENOXYETHANOL; METHYLPARABEN; GLYCERYL MONOSTEARATE; XANTHAN GUM; ETHYLPARABEN; PROPYLPARABEN; POTASSIUM HYDROXIDE; EDETATE TRISODIUM; FD&C YELLOW NO. 5; FD&C YELLOW NO. 6

Drug Fact

ACTIVE INGREDIENT

OCTINOXATE 7%

TITANIUM DIOXIDE 6%

OCTISALATE 4.8%

ENSULIZOLE 3.9%

BIS-ETHYLHEXYLOXYPHENOL METHOXYPHENYL TRIAZINE 0.5%

WARNINGS AND PRECAUTIONS

For external use only.

Keep out of reach of children. Is swallowed, get medical help or contact a Poison Control Center right away.

WHEN USING

Keep out of eyes. Rinse with water to remove.